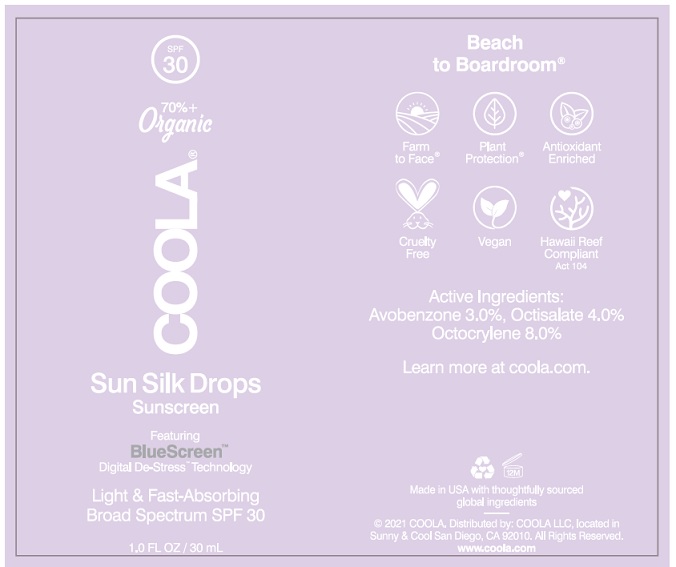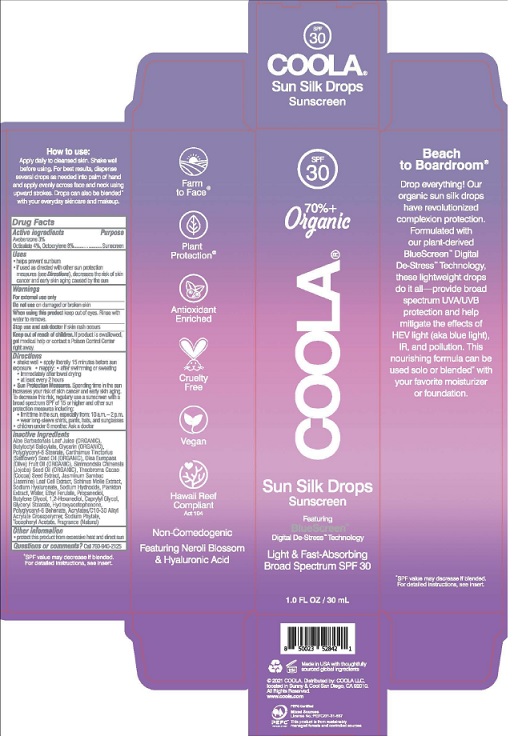 DRUG LABEL: COOLA Sun Silk Drops SPF 30
NDC: 79753-038 | Form: LIQUID
Manufacturer: COOLA LLC
Category: otc | Type: HUMAN OTC DRUG LABEL
Date: 20210507

ACTIVE INGREDIENTS: AVOBENZONE 3.0 g/100 mL; OCTISALATE 4.0 g/100 mL; OCTOCRYLENE 8.0 g/100 mL
INACTIVE INGREDIENTS: ALOE VERA LEAF; BUTYLOCTYL SALICYLATE; GLYCERIN; POLYGLYCERYL-6 STEARATE; SAFFLOWER SEED OIL POLYGLYCERYL-6 ESTERS; OLIVE OIL; JOJOBA OIL; COCOA; JASMINUM SAMBAC FLOWER; SCHINUS MOLLE FRUITING TOP; HYALURONATE SODIUM; SODIUM HYDROXIDE; ARTHROSPIRA PLATENSIS; WATER; ETHYL FERULATE; PROPANEDIOL; BUTYLENE GLYCOL; 1,2-HEXANEDIOL; CAPRYLYL GLYCOL; GLYCERYL MONOSTEARATE; HYDROXYACETOPHENONE; POLYGLYCERYL-6 BEHENATE; CARBOMER INTERPOLYMER TYPE A (ALLYL SUCROSE CROSSLINKED); PHYTATE SODIUM; .ALPHA.-TOCOPHEROL ACETATE

COOLA Sun Silk Drops SPF 30

Drug Facts

Active Ingredients

Avobenzone 3%, Octisalate 4%, Octocrylene 8%

Purpose

Suncreen

Uses

- helps prevent sunburn

- if used as directed with other sun protection

measures (see Directions), decreases the risk of skin

cancer and early skin aging caused by the sun

Warnings

For external use only

Do not use on damaged or broken skin

When using this product keep out of eyes. Rinse with

water to remove.

Stop use and ask doctor if skin rash occurs

Keep out of reach of children. If product is swallowed,

get medical help or contact a Poison Control Center

right away.

Directions
● shake well ● apply liberally 15 minutes before sun
exposure • reapply: ● after 80 minutes of swimming or sweating
● immediately after towel drying
● at least every 2 hours
● Sun Protection Measures. Spending time in the sun
increases your risk of skin cancer and early skin aging.
To decrease this risk, regularly use a sunscreen with a
broad spectrum SPF of 15 or higher and other sun
protection measures including:
● limit time in the sun, especially from: 10 a.m. - 2 p.m.
● wear long-sleeve shirts, pants, hats, and sunglasses
● Children under 6 months: Ask a doctor

Inactive Ingredients
Aloe Barbadensis Leaf Juice (ORGANIC),
Butyloctyl Salicylate, Glycerin (ORGANIC),
Polyglyceryl-6 Stearate, Carthamus Tinctorius
(Safflower) Seed Oil (ORGANIC), Olea Europaea
(Olive) Fruit Oil (ORGANIC), Simmondsia Chinensis
(Jojoba) Seed Oil (ORGANIC), Theobroma Cacao
(Cocoa) Seed Extract, Jasminum Sambac
(Jasmine) Leaf Cell Extract, Schinus Molle Extract,
Sodium Hyaluronate, Sodium Hydroxide, Plankton
Extract, Water, Ethyl Ferulate, Propanediol,
Butylene Glycol, 1,2-Hexanedipol, Caprylyl Glycol,
Glyceryl Stearate, Hydroxyacetophenone,
Polyglyceryl-6 Behenate, Acrylates/10-30 Alkyl
Acrylate Crosspolymer, Sodium Phylae,
Tocopheryl Acetate, Fragrance (Natural)

Other information

- protect this product from excessive heat and direct sun

Questions or comments? Call 760-940-2125

COOLA Label

SPF

30

70%+

Organic

COOLA®

Sun Silk Drops

Sunscreen

1.0 FL OZ / 30 mL

*SPF value may decrease if blended.

For detailed instructions, see insert.

©2021 COOLA. Distributed by: COOLA LLC,

located in Sunny & Cool San Diego, CA 92010.

All Rights Reserved.

www.coola.com

Carton

Bottle

res